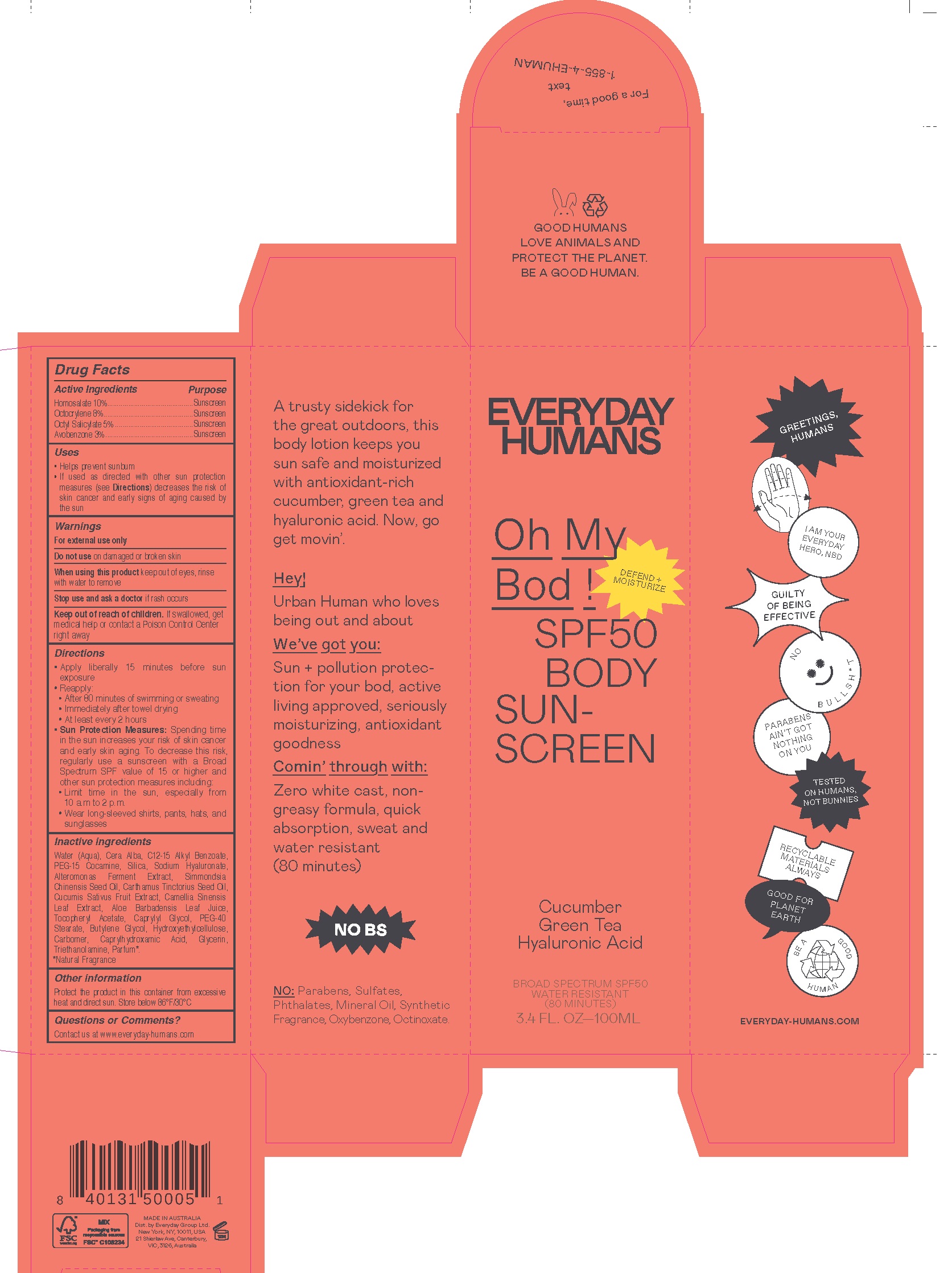 DRUG LABEL: Oh My Bod SPF50 Antioxidant Infused Dry Touch Sunscreen
NDC: 72098-002 | Form: CREAM
Manufacturer: Everyday Group Limted
Category: otc | Type: HUMAN OTC DRUG LABEL
Date: 20251204

ACTIVE INGREDIENTS: AVOBENZONE 30 mg/1 mL; HOMOSALATE 100 mg/1 mL; OCTOCRYLENE 80 mg/1 mL; OCTISALATE 50 mg/1 mL
INACTIVE INGREDIENTS: GREEN TEA LEAF; CAPRYLHYDROXAMIC ACID; WATER; WHITE WAX; ALKYL (C12-15) BENZOATE; PEG-15 COCAMINE; SILICON DIOXIDE; CAPRYLYL GLYCOL; PEG-40 STEARATE; CARBOXYPOLYMETHYLENE; TROLAMINE; ALOE VERA LEAF; .ALPHA.-TOCOPHEROL ACETATE; JOJOBA OIL; SAFFLOWER OIL; GLYCERIN

Oh My Bod! SPF50 Antioxidant Infused Dry Touch Sunscreen

Active ingredients

Butyl Methoxydibenzoylmethane 3%

Homosalate 10%

Octocrylene 8%

Octyl Salicylate 5%

Purpose

Sunscreen

Uses

- Helps prevent sunburn
- if used as directed with other sun protection measures (see) decreases the risk of skin cancer and early skin aging caused by the sun Directions

Warnings

For external use only

Do not use

on damaged or broken skin

When using this product

keep out of eyes, rinse with water to remove

Stop use and ask a doctor

if rash occurs

Keep out of reach of children.

If swallowed, get medical help or contact a Poison Control Center right away

Directions

- Apply liberally 15 minutes before sun exposure
- Reapply:
- After 80 minutes of swimming or sweating
- Immediately after towel drying
- At least every 2 hours
- Sun Protection Measures: Spending time in the sun increases your risk of skin cancer and early skin aging. To decrease this risk, regularly use a sunscreen with a Broad Spectrum SPF value of 15 or higher and other sun protection measures including:
- Limit time in the sun, especially from 10 a.m. - 2 p.m.
- Wear long-sleeved shirts, pants, hats, and sunglasses

Other information

Protect the product in this container from excessive heat and direct sun.

Inactive ingredients

Water (Aqua), Cera Alba, C12-15 Alkyl Benzoate, PEG-15 Cocamine, Silica, Caprylyl Glycol, PEG-40 Stearate, Hydroxyethylcellulose, Carbomer, Triethanolamine, Aloe Barbadnesis Leaf Juice, Tocopheryl Acetate, Simmondsia Chinensis Seed Oil, Glycerin, Carthamus Tinctorius Seed Oil, Cucumis Sativus Fruit Extract, Camellia Sinensis Leaf Extract, Caprylhydroxamic Acid